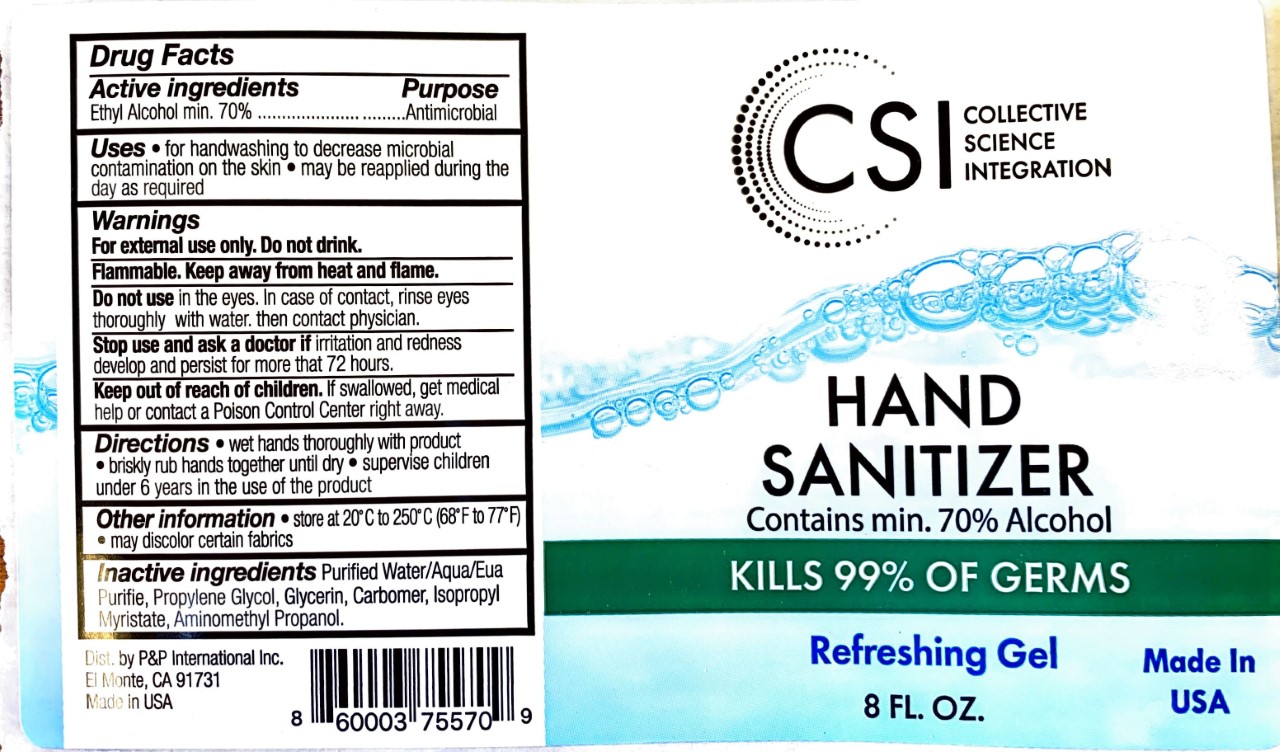 DRUG LABEL: P P International Inc.
NDC: 77356-989 | Form: GEL
Manufacturer: Adonis, LLC.
Category: otc | Type: HUMAN OTC DRUG LABEL
Date: 20200807

ACTIVE INGREDIENTS: ALCOHOL 70 mL/100 mL
INACTIVE INGREDIENTS: WATER; PROPYLENE GLYCOL; CARBOMER HOMOPOLYMER, UNSPECIFIED TYPE; ISOPROPYL MYRISTATE; AMINOMETHYLPROPANOL; GLYCERIN

Collective Science Integration -Hand Sanitizer

Active Ingredient(s)

Ethyl Alcohol 70% v/v. .......... Antimicrobial

Purpose

Antimicrobial, Hand Sanitizer

Use

- For handwashing to decrease microbial contamination on the skin
- May be reapplied during the day as required.

Warnings

For external use only. Flammable. Keep away from heat or flame

Do not Drink.

Do not use

- In the eyes
- In case of contact,rinse eyes thoroughly with water.
- Then contact physician.

When using this product avoid contact with eyes. If contact occurs, rinse rinse eyes thoroughly with water.

Stop use and ask a doctor if irritation or redness devleops and persist for more that 72 hours.

Keep out of reach of children. If swallowed, get medical help or contact a Poison Control Center right away.

Directions

- Wet hands thoroughly with product
- Briskly rub hands together until dry
- Supervise children under 6 years of age when using this product to avoid swallowing.

Other information

- Store between 20ºC to 250ºC(68ºF-77ºF)
- May discolor certain fabrics

Inactive ingredients

Glycerin, Water ,Propylene Glycol, Carbomer ,Aminomethyl Propanol,Isopropyl Myristate.